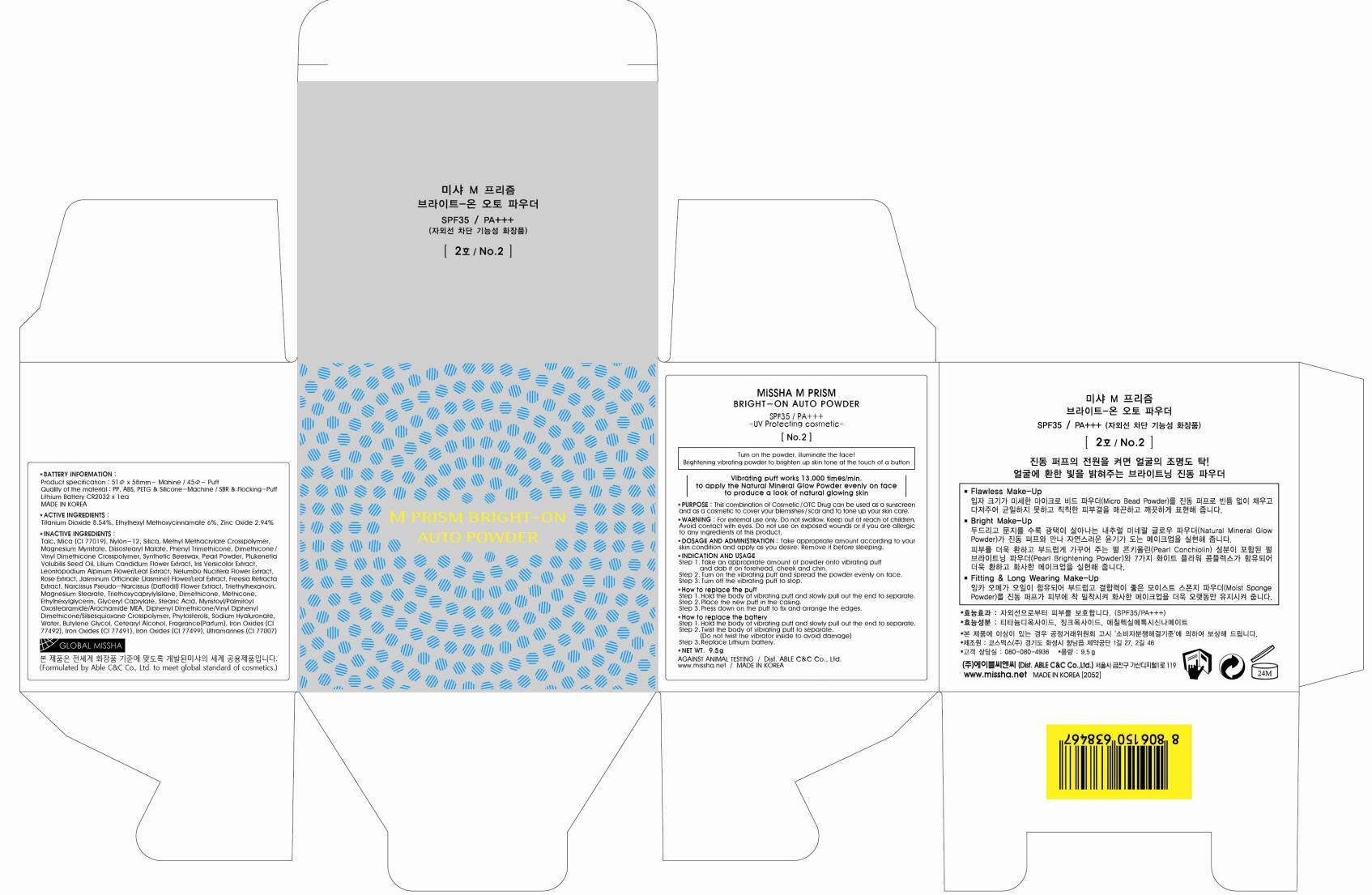 DRUG LABEL: MISSHA M PRISM BRIGHT ON AUTO
NDC: 13733-017 | Form: POWDER
Manufacturer: ABLE C&C CO., LTD.
Category: otc | Type: HUMAN OTC DRUG LABEL
Date: 20121029

ACTIVE INGREDIENTS: Titanium Dioxide 0.81 g/9.5 g; OCTINOXATE 0.57 g/9.5 g; Zinc Oxide 0.28 g/9.5 g
INACTIVE INGREDIENTS: Talc; Mica; Magnesium Myristate; Dimethicone

ACTIVE INGREDIENT

ACTIVE INGREDIENTS: Titanium Dioxide 8.54%, Ethylhexyl Methoxycinnamate 6%, Zinc Oxide 2.94%

INACTIVE INGREDIENT

INACTIVE INGREDIENTS:
Talc, Mica, Nylon-12, Silica, Methyl Methacrylate Crosspolymer, Magnesium Myristate, Diisostearyl Malate, Phenyl Trimethicone, Dimethicone/Vinyl Dimethicone Crosspolymer, Synthetic Beeswax, Pearl Powder, Plukenetia Volubilis Seed Oil, Lilium Candidum Flower Extract, Iris Versicolor Extract, Leontopodium Alpinum Flower/Leaf Extract, Nelumbo Nucifera Flower Extract, Rose Extract, Jasminum Officinale (Jasmine) Flower/Leaf Extract, Freesia Refracta Extract, Narcissus Pseudo-Narcissus (Daffodil) Flower Extract, Triethylhexanoin, Magnesium Stearate, Triethoxycaprylylsilane, Dimethicone, Methicone, Ethylhexylglycerin, Glyceryl Caprylate, Stearic Acid, Myristoyl/Palmitoyl Oxostearamide/Arachamide MEA, Diphenyl Dimethicone/Vinyl Diphenyl Dimethicone/Silsesquioxane Crosspolymer, Phytosterols, Sodium Hyaluronate, Water, Butylene Glycol, Cetearyl Alcohol, Fragrance(Parfum), Iron Oxides

PURPOSE

PURPOSE: This combination of Cosmetic / OTC Drug can be used as a sunscreen and as a cosmetic to cover your blemishes / scar and to tone up your skin care.

WARNINGS

WARNING:
For external use only.
Do not swallow.
Keep out of reach of children.
Avoid contact with eyes.
Do not use on exposed wounds or if you are allergic to any ingredients of this product.

KEEP OUT OF REACH OF CHILDREN

INDICATIONS AND USAGE

INDICATION AND USAGE:
Step 1. Take an appropriate amount of powder onto vibrating puff and dab it on forehead, cheek and chin.
Step 2. Turn on the vibrating puff and spread the powder evenly on face.
Step 3. Turn off the vibrating puff to stop.

- How to replace the puff
Step 1. Hold the body of vibrating puff and slowly pull out the end to separate.
Step 2. Place the new puff in the casing.
Step 3. Press down on the puff to fix and arrange the edges.

- How to replace the battery
Step 1. Hold the body of vibrating puff and slowly pull out the end to separate.
Step 2. Twist the body of vibrating puff to separate. (Do not twist the vibrator inside to avoid damage)
Step 3. Replace Lithium battery.

DOSAGE AND ADMINISTRATION

Take appropriate amount according to your skin condition and apply as you desire.
Remove it before sleeping.